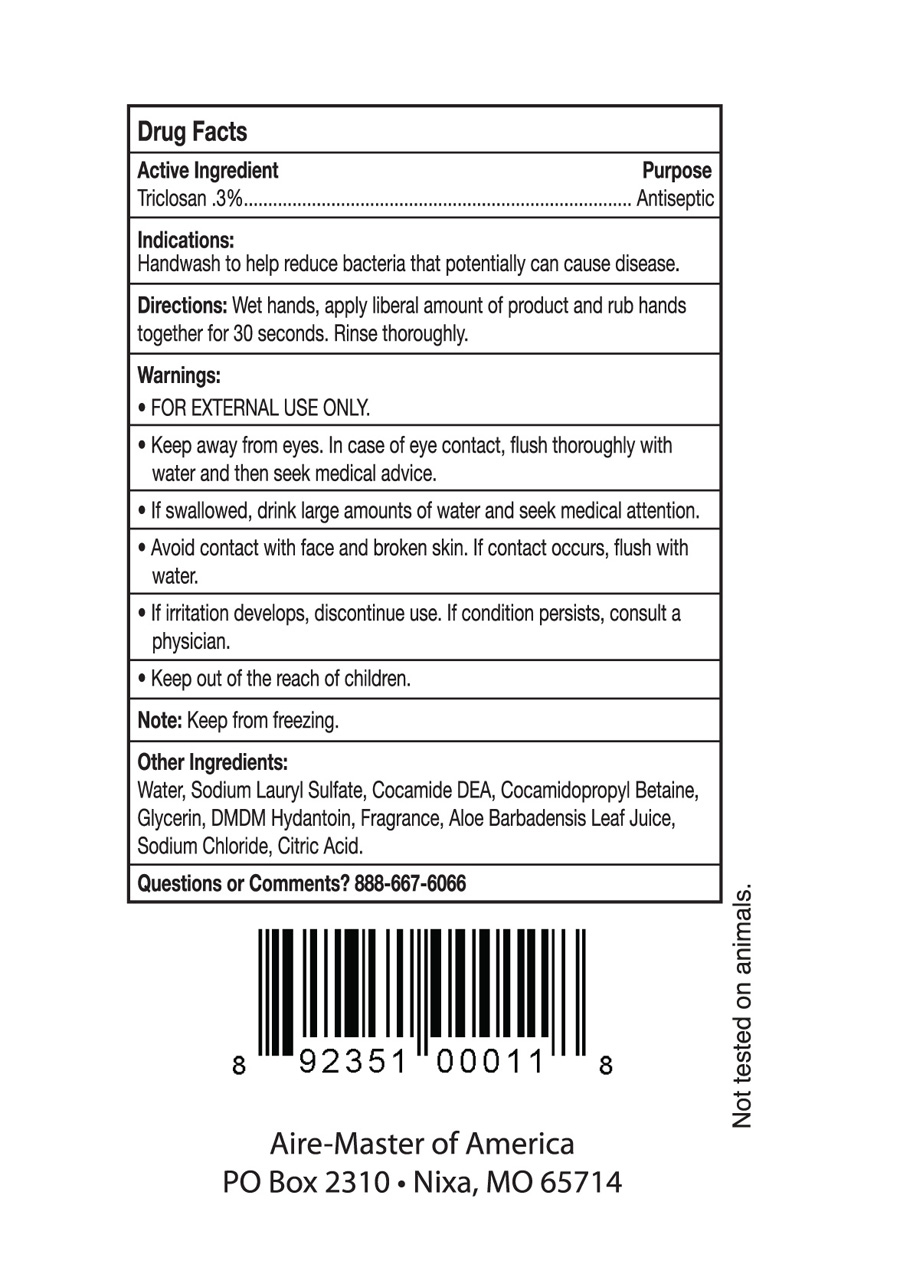 DRUG LABEL: Aire-Master
NDC: 65133-170 | Form: LIQUID
Manufacturer: Aire-Master of America, Inc.
Category: otc | Type: HUMAN OTC DRUG LABEL
Date: 20200129

ACTIVE INGREDIENTS: TRICLOSAN 0.3 g/10 mL
INACTIVE INGREDIENTS: WATER; TRIETHANOLAMINE LAURYL SULFATE; COCAMIDOPROPYL BETAINE; COCO DIETHANOLAMIDE; GLYCERIN; DMDM HYDANTOIN; PROPYLENE GLYCOL; ALOE VERA LEAF

Drug Facts

Active Ingredient

Triclosan .3%

Purpose

Antiseptic

INDICATIONS AND USAGE

Uses Handwash to help reduce bacteria that potentially can cause disease

Warnings For external use only

Do not use in eyes. In case of eye contact flush thoroughly with water and seek medical attention.

Stop use and ask doctor if irritation and redness develop and persists for more than 72 hours.

Keep out of reach of children. If swallowed, get medical help or contact a Poison Control Center

right away.

DOSAGE AND ADMINISTRATION

Directions -Wet hands, apply liberal amount of product and rub hands together for 30 seconds.

-Rinse thoroughly.

Other Information -Keep from freezing.

INACTIVE INGREDIENT

Inactive Ingredients Water, TEA Lauryl Sulfate, Cocamidopropyl Betaine, Cocamide

DEA, Glycerin, Fragrance, DMDM Hydantoin, Propylene Glycol, Aloe Barbadensis Leaf Juice.

Questions or Comments? 800-525-0957 www.airemaster.com